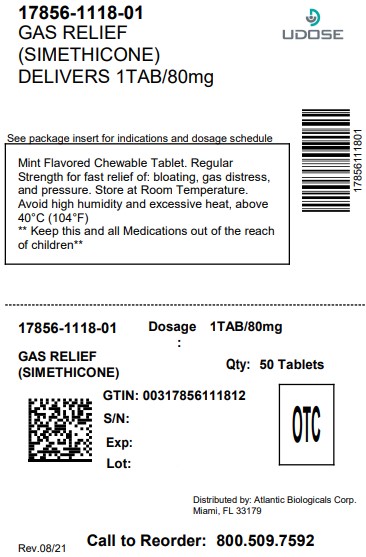 DRUG LABEL: GNP Regular Strength Gas Relief
NDC: 17856-1118 | Form: TABLET, CHEWABLE
Manufacturer: ATLANTIC BIOLOGICALS CORP.
Category: otc | Type: HUMAN OTC DRUG LABEL
Date: 20250624

ACTIVE INGREDIENTS: DIMETHICONE 80 mg/1 1
INACTIVE INGREDIENTS: RAW SUGAR; DEXTROSE; MAGNESIUM STEARATE; MALTODEXTRIN; CELLULOSE, MICROCRYSTALLINE; SORBITOL

GNP Gas Relief

Active ingredient (in each tablet)

Simethicone 80 mg

Purpose

Antigas

HOW SUPPLIED

NDC 17856-1118-1

regular strength

Gas Relief

Anti-gas

fast relief of: pressure, bloating & gas distress

mint

50 chewable tablets (80 mg ea.)

Uses

relieves:

- pressure
- bloating
- symptoms referred to as gas

Warnings

Keep out of reach of children.In case of overdose, get medical help or contact a poison control center immediately.

Directions

- chew 2 to 4 tablets thoroughly as needed after meals and at bedtime.
- do not exceed 6 tablets per day unless directed by a physician.

Other information

- do not use if inner seal is broken.
- store at room temperature
- avoid high humidity and excessive heat, above 40^0C (104^0F)

Inactive ingredients

compressible sugar, dextrose, flavor, magnesium stearate, maltodextrin, microcrystalline cellulose, sorbitol

DISTRIBUTED BY:

ATLANTIC BIOLOGICALS CORP.

MIAMI, FL 33179